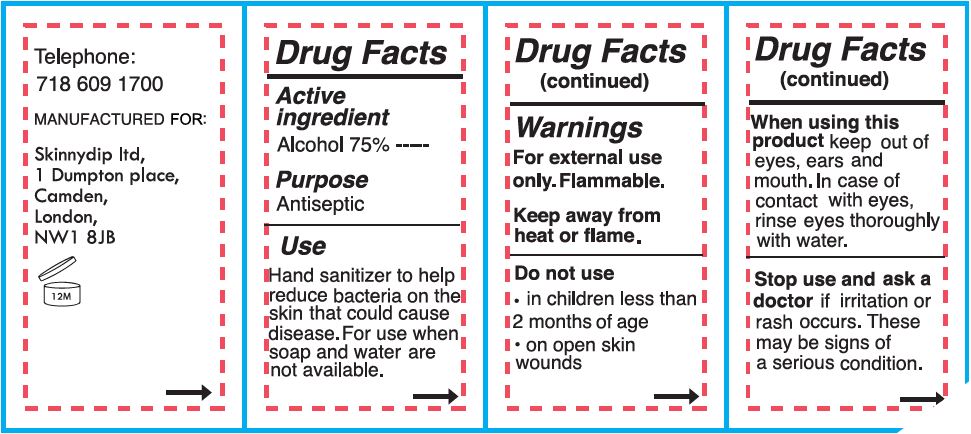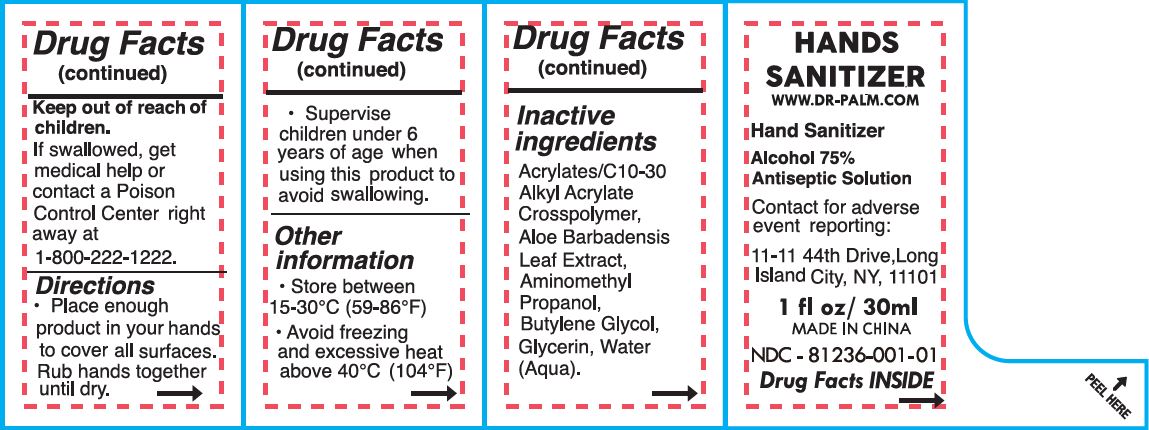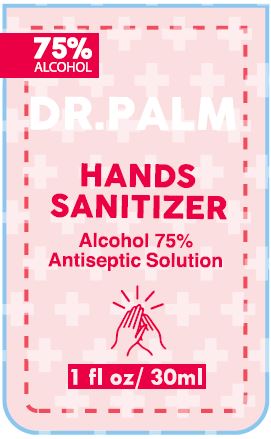 DRUG LABEL: HAND SANITIZER
NDC: 81886-101 | Form: GEL
Manufacturer: Frog Prince (Fujian) Baby & Child Care Products Co., Ltd.
Category: otc | Type: HUMAN OTC DRUG LABEL
Date: 20210513

ACTIVE INGREDIENTS: ALCOHOL 75 mL/100 mL
INACTIVE INGREDIENTS: CARBOMER HOMOPOLYMER, UNSPECIFIED TYPE; ALOE VERA FLOWER; AMINOMETHYLPROPANOL; BUTYLENE GLYCOL; GLYCERIN; WATER

DR. PALM HAND SANITIZER - ALCOHOL 75% - ANTISEPTIC SOLUTION

ACTIVE INGREDIENT

ALCOHOL 75%

PURPOSE

ANTISEPTIC

USE

HAND SANITIZER TO HELP REDUCE BACTERIA ON THE SKIN THAT COULD CAUSE DISEASE. FOR USE WHEN SOAP AND WATER ARE NOT AVAILABLE.

WARNINGS

FOR EXTERNAL USE ONLY.

KEEP AWAY FROM HEAT OR FLAME.

DO NOT USE

- IN CHILDREN LESS THAN 2 MONTHS OF AGE
- ON OPEN SKIN WOUNDS

WHEN USING THIS PRODUCT KEEP OUT OF EYES, EARS AND MOUTH. IN CASE OF CONTACT WITH EYES, RINSE EYES THOROUGHLY WITH WATER.

STOP USE AND ASK A DOCTOR IF IRRITATION OR RASH OCCURS. THESE MAY BE SIGNS OF A SERIOUS CONDITION.

KEEP OUT OF REACH OF CHILDREN.

IF SWALLOWED, GET MEDICAL HELP OR CONTACT A POISON CONTROL CENTER RIGHT AWAY AT 1-800-222-1222.

DIRECTIONS

- PLACE ENOUGH PRODUCT IN YOUR HANDS TO COVER ALL SURFACES. RUB HANDS TOGETHER UNTIL DRY.
- SUPERVISE CHILDREN UNDER 6 YEARS OF AGE WHEN USING THIS PRODUCT TO AVOID SWALLOWING.

OTHER INFORMATION

- STORE BETWEEN 15-30°C (59-86°F)
- AVOID FREEZING AND EXCESSIVE HEAT ABOVE 40°C (104°F)

INACTIVE INGREDIENTS

ACRYLATES/C10-30 ALKYL ACRYLATE CROSSPOLYMER, ALOE BARBADENSIS LEAF EXTRACT, AMINOMETHYL PROPANOL, BUTYLENE GLYCOL, GLYCERIN, WATER (AQUA).